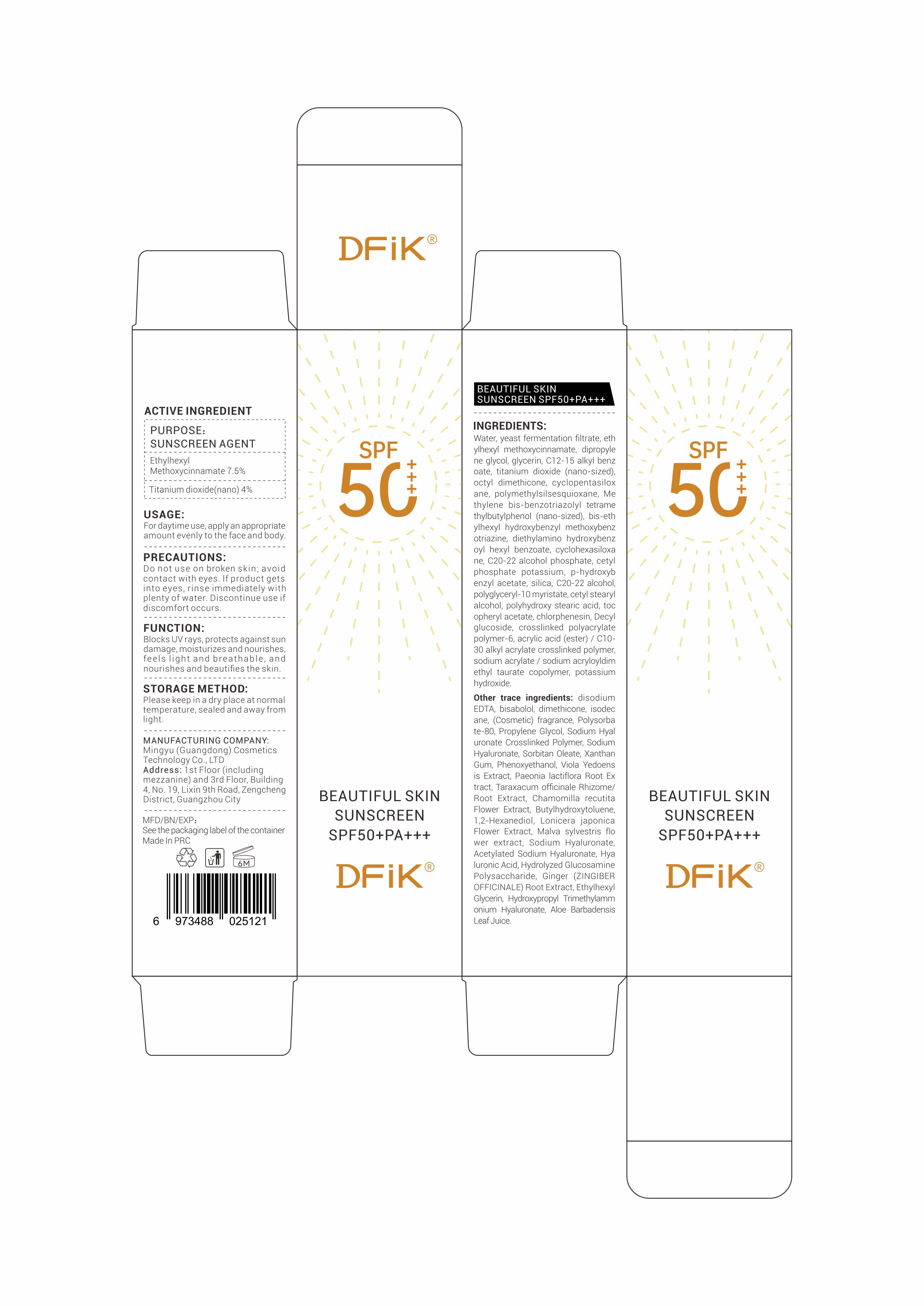 DRUG LABEL: sunscreen
NDC: 87091-001 | Form: LOTION
Manufacturer: Mingyu (guangdong) Cosmetics Technology Co., Ltd
Category: otc | Type: HUMAN OTC DRUG LABEL
Date: 20250910

ACTIVE INGREDIENTS: TITANIUM DIOXIDE 4 g/100 g; ETHYLHEXYL METHOXYCINNAMATE 7.5 g/100 g
INACTIVE INGREDIENTS: CAPRYLYL METHICONE; POLYMETHYLSILSESQUIOXANE (4.5 MICRONS); METHYLENE BIS-BENZOTRIAZOLYL TETRAMETHYLBUTYLPHENOL; LONICERA JAPONICA FLOWER; GINGER; C12-15 ALKYL BENZOATE; SODIUM ACRYLATE/SODIUM ACRYLOYLDIMETHYLTAURATE COPOLYMER (4000000 MW); AQUA; POLYHYDROXYSTEARIC ACID (2300 MW); CYCLOHEXASILOXANE; DECYL GLUCOSIDE; DIETHYLAMINO HYDROXYBENZOYL HEXYL BENZOATE; MALVA SYLVESTRIS WHOLE; HYDROLYZED GLYCOSAMINOGLYCANS (BOVINE; 50000 MW); DIPROPYLENE GLYCOL; SACCHAROMYCES LYSATE; VIOLA PHILIPPICA WHOLE; TARAXACUM OFFICINALE (DANDELION) ROOT; POLYACRYLATE CROSSPOLYMER-6; DIMETHICONE; SORBITAN OLEATE; PEG-9 DIGLYCIDYL ETHER/SODIUM HYALURONATE CROSSPOLYMER; SODIUM HYALURONATE; XANTHAN GUM; CHAMOMILE; BHT; CYCLOPENTASILOXANE; SODIUM ACETYLATED HYALURONATE; ETHYLHEXYLGLYCERIN; POTASSIUM HYDROXIDE; BISABOLOL; CHLORPHENESIN; ISOHEXADECANE; HYALURONIC ACID; ALOE BARBADENSIS LEAF JUICE; POTASSIUM CETYL PHOSPHATE; ACRYLATES/C10-30 ALKYL ACRYLATE CROSSPOLYMER (60000 MPA.S); PAEONIA LACTIFLORA ROOT; POLYGLYCERYL-10 MYRISTATE; CETEARYL ALCOHOL; C20-22 ALKYL PHOSPHATE; HYDROXYACETOPHENONE; GLYCERIN; EDETATE DISODIUM; POLYSORBATE 80; PROPYLENE GLYCOL; 1,2-HEXANEDIOL; SILICA; BIS-ETHYLHEXYLOXYPHENOL METHOXYPHENYL TRIAZINE; PHENOXYETHANOL; ALPHA-TOCOPHEROL ACETATE; C20-22 ALCOHOLS

INACTIVE INGREDIENT

WATER
SACCHAROMYCES FERMENT FILTRATE
DIPROPYLENE GLYCOL
GLYCERIN
C12-15 ALKYL BENZOATE
CAPRYLYL METHICONE
CYCLOPENTASILOXANE
POLYMETHYLSILSESQUIOXANE
METHYLENE BIS-BENZOTRIAZOLYL
TETRAMETHYLBUTYLPHENOL(NANO)
BIS-ETHYLHEXYLOXYPHENOL METHOXYPHENYL
TRIAZINE
DIETHYLAMINO HYDROXYBENZOYL HEXYL
BENZOATE
CYCLOHEXASILOXANE
C20-22 ALKYL PHOSPHATE
POTASSIUM CETYL PHOSPHATE
HYDROXYACETOPHENONE
SILICA
C20-22 ALCOHOLS
POLYGLYCERYL-10 MYRISTATE
CETEARYL ALCOHOL
POLYHYDROXYSTEARIC ACID
TOCOPHERYL ACETATE
CHLORPHENESIN
DECYL GLUCOSIDE
POLYACRYLATE CROSSPOLYMER-6
ACRYLATES/C10-30 ALKYL ACRYLATE CROSSPOLYMER
SODIUM ACRYLATE/SODIUM
ACRYLOYLDIMETHYL TAURATE COPOLYMER
POTASSIUM HYDROXIDE
DISODIUM EDTA
BISABOLOL
DIMETHICONE
ISOHEXADECANE
POLYSORBATE 80
PROPYLENE GLYCOL
SODIUM HYALURONATE CROSSPOLYMER
SODIUM HYALURONATE
SORBITAN OLEATE
XANTHAN GUM
PHENOXYETHANOL
VIOLA YEDOENSIS EXTRACT
PAEONIA LACTIFLORA ROOT EXTRACT
TARAXACUM OFFICINALE (DANDELION)
RHIZOME/ROOT EXTRACT
CHAMOMILLA RECUTITA (MATRICARIA)
FLOWER EXTRACT
BHT
1,2-HEXANEDIOL
LONICERA JAPONICA (HONEYSUCKLE) FLOWER EXTRACT
MALVA SYLVESTRIS (MALLOW) FLOWER
EXTRACT
HYDROLYZED SODIUM HYALURONATE
SODIUM ACETYLATED HYALURONATE
HYALURONIC ACID
HYDROLYZED GLYCOSAMINOGLYCANS
ZINGIBER OFFICINALE (GINGER) ROOT
EXTRACT
ETHYLHEXYLGLYCERIN
HYDROXYPROPYLTRIMONIUM HYALURONATE
ALOE BARBADENSIS LEAF JUICE

ACTIVE INGREDIENT

ETHYLHEXYL METHOXYCINNAMATE 7.5%

TITANIUM DIOXIDE(NANO) 4%

DOSAGE AND ADMINISTRATION

USAGE：For daytime use, apply an appropriate amount evenly to the face and body.

WARNINGS

PRECAUTIONS:
Do not use for food purposes.Do not use on broken skin; avoid contact with eyes.
If product gets into eyes, rinse immediately with plenty of water. Discontinue use if discomfort occurs.

INDICATIONS AND USAGE

FUNCTION:
Blocks UV rays. protects against sun damage, moisturizes and nourishes,
feels light and breathable, and nourishes and beautifies the skin.

KEEP OUT OF REACH OF CHILDREN

Keep out of eyes: In case of contact with eyes, please fush thoroughly with water.

PURPOSE

Sun Protection